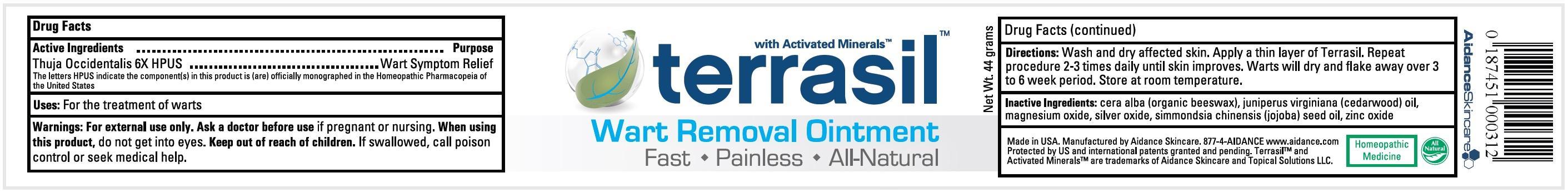 DRUG LABEL: Terrasil Wart Removal
NDC: 24909-127 | Form: OINTMENT
Manufacturer: Aidance Skincare & Topical Solutions, LLC
Category: homeopathic | Type: HUMAN OTC DRUG LABEL
Date: 20140228

ACTIVE INGREDIENTS: THUJA OCCIDENTALIS LEAFY TWIG 6 [hp_X]/1 g
INACTIVE INGREDIENTS: JOJOBA OIL; JUNIPERUS VIRGINIANA OIL; MAGNESIUM OXIDE; SILVER OXIDE; WHITE WAX; ZINC OXIDE

Drug Facts

Active Ingredient

Thuja Occidentalis

The letters HPUS indicate the component(s) in this product is (are) officially monographed in the Homeopathic Pharmacopeia of the United States

Purpose

Wart Symptom Relief

Uses

For the treatment of warts

Warnings

For external use only.
Ask a doctor before use if pregnant or nursing.
When using this product, do not get into eyes.

Keep out of reach of children.

If swallowed, call poison control or seek medical help.

Directions

Wash and dry affected skin. Apply a thin layer of Terrasil. Repeat procedure 2-3 times daily until skin improves. Warts will dry and flake away over 3 to 6 week period. Store at room temperature.

Inactive Ingredients

cera alba (organic beeswax), juniperus virginiana (cedarwood) oil, silver oxide, magnesium oxide, simmondsia chinensis (jojoba) seed oil, zinc oxide

PRINCIPAL DISPLAY PANEL - 44g Label

terrasil

Wart Removal
Fast - Painless - All-Natural